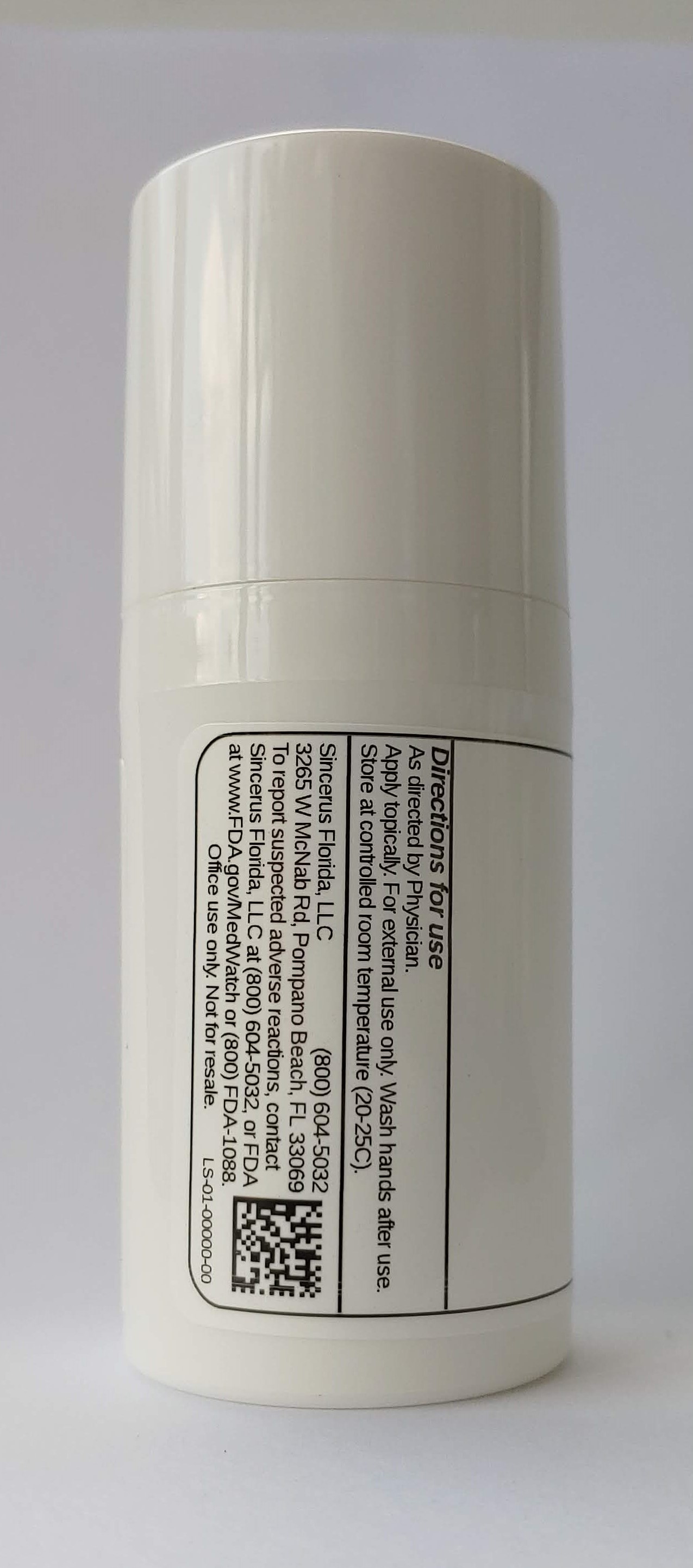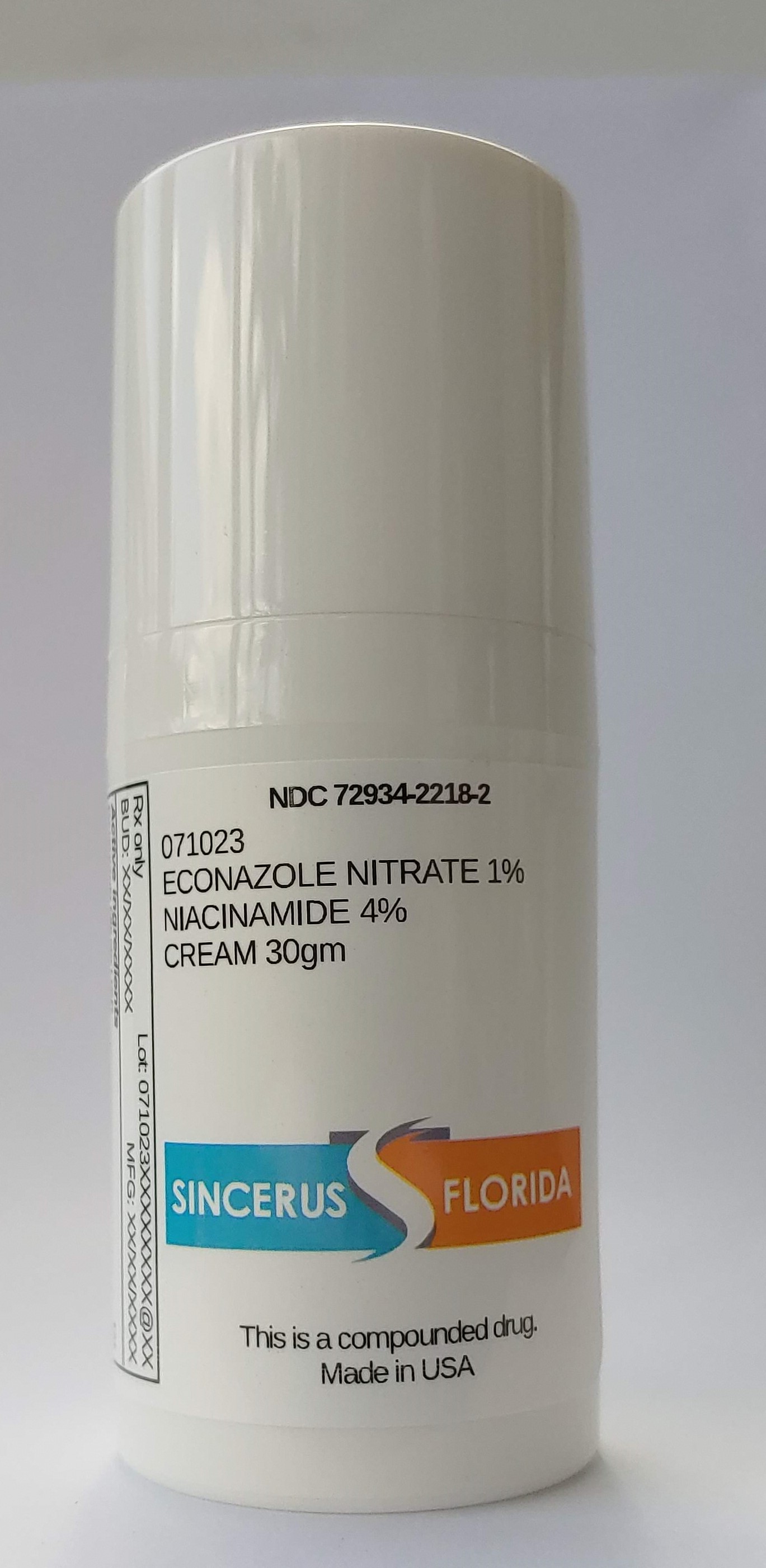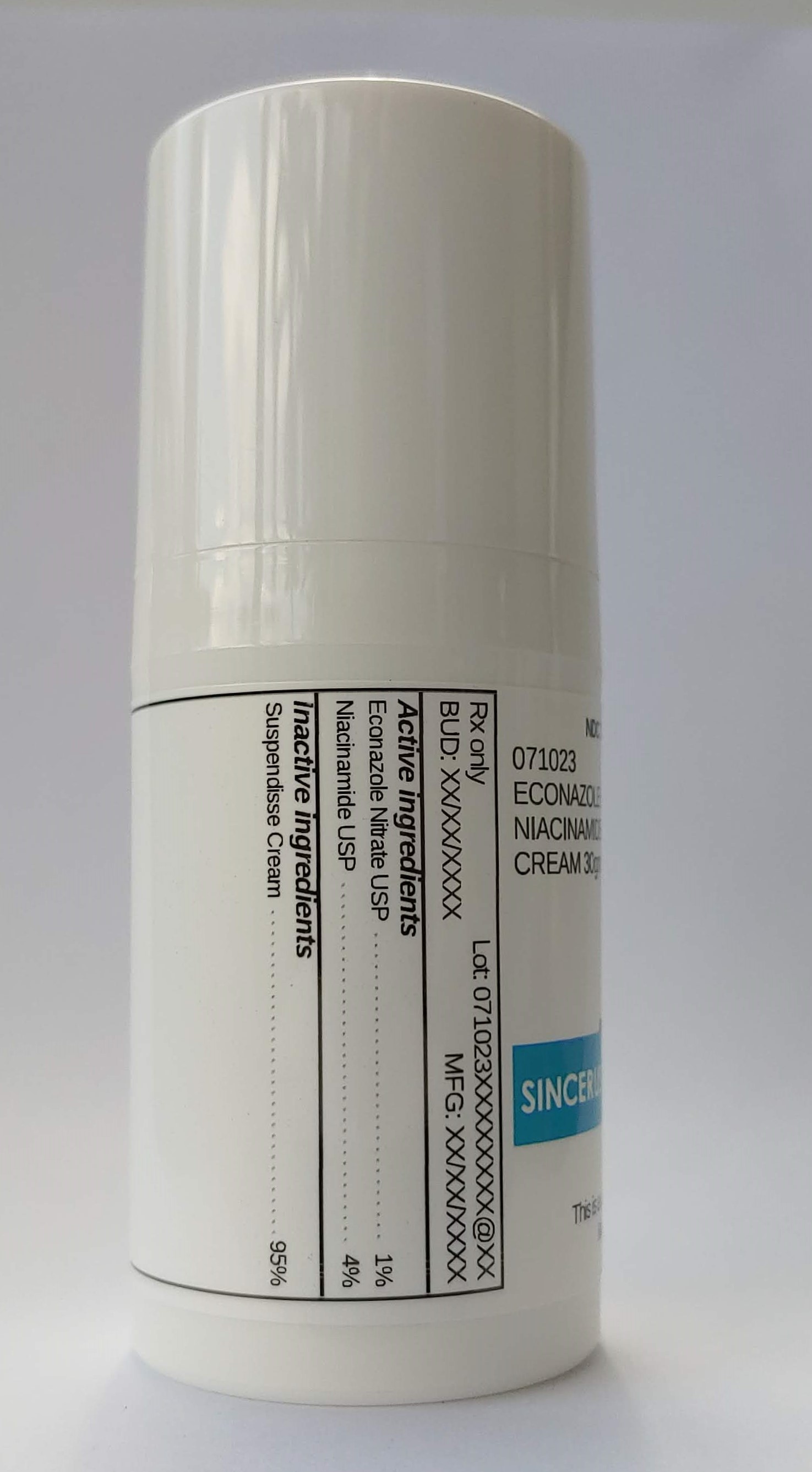 DRUG LABEL: 071023 ECONAZOLE NITRATE 1% / NIACINAMIDE 4%
NDC: 72934-2218 | Form: CREAM
Manufacturer: Sincerus Florida, LLC
Category: prescription | Type: HUMAN PRESCRIPTION DRUG LABEL
Date: 20200702

ACTIVE INGREDIENTS: ECONAZOLE NITRATE 1 g/100 g; NIACINAMIDE 4 g/100 g

071023 ECONAZOLE NITRATE 1% / NIACINAMIDE 4%